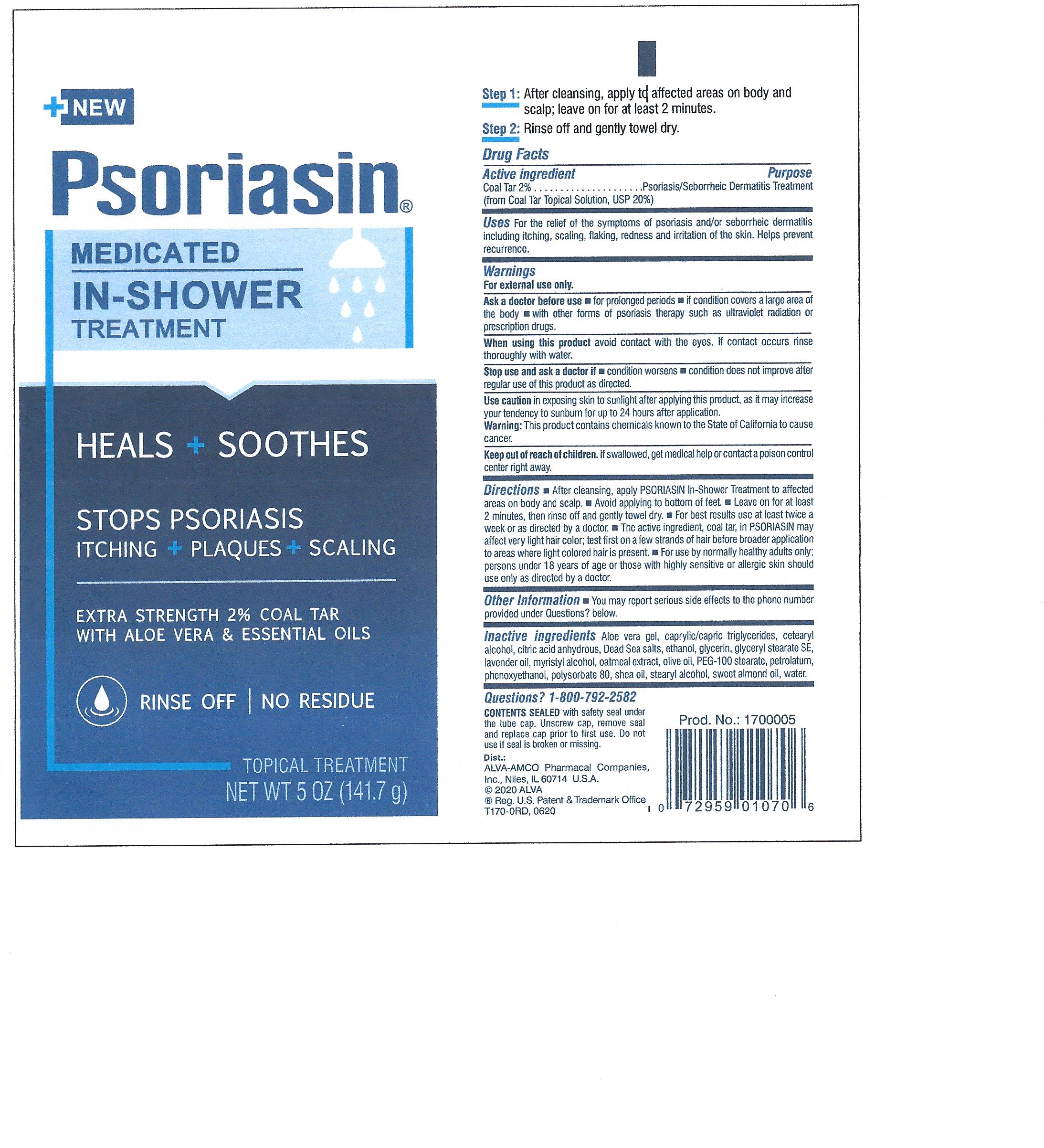 DRUG LABEL: Psoriasin In-Shower
NDC: 52389-670 | Form: LOTION/SHAMPOO
Manufacturer: Kobayashi Healthcare International, Inc.
Category: otc | Type: HUMAN OTC DRUG LABEL
Date: 20251219

ACTIVE INGREDIENTS: COAL TAR 20 mg/1 g
INACTIVE INGREDIENTS: ALCOHOL; GLYCERIN; WATER; ALOE VERA LEAF; POLYSORBATE 80; CETEARYL BEHENATE; ANHYDROUS CITRIC ACID; STEARYL ALCOHOL; ALOE VERA LEAF POLYSACCHARIDES; CAPRYLIC/CAPRIC/LINOLEIC TRIGLYCERIDE; GLYCERYL STEARATE SE; ALMOND OIL; LAVENDER OIL; MYRISTYL ALCOHOL; OATMEAL; OLIVE OIL; PEG-100 STEARATE; WHITE PETROLATUM; PHENOXYETHANOL; SHEANUT OIL

Psoriasin In-Shower Treatment

Active Ingredient

Coal Tar 2% (from Coal Tar Topical Solution, USP 20%)

Purpose

Psoriasis / Seborrheic Dermatitis Treatment

Uses

For the relief of symptoms of psoriasis and/or seborrheic dermatitis including itching, scaling, flaking, redness and irriation of the skin. Helps prevent recurrence.

Warnings

For external use only.

Ask a doctor before use

- for prolonged periods
- if condition covers a large area of the body
- with other forms of psoriasis therapy such as ultraviolet radiation or prescription drugs

When using this product

avoid contact with the eyes. If contact occurs rinse thoroughly with water.

Stop use and ask a doctor if

- condition worsens
- condition does not improve after regular use of this product as directed.

Use caution

in exposing skin to sunlight after applying this product, as it may increase your tendency to sunburn for up to 24 hours after application.

Warning: This product contains chemicals known to the State of California to cause cancer.

Keep out of reach of children.

If swallowed, get medical help or contact a poison control cente right away.

Directions

After cleansing, apply Psoriasin In-Shower Treatment to affected areas on body and scalp. Avoid applying to bottom of feet. Leave on for at least 2 minutes, then rinse off and gently towel dry. For best results, use at least twice a week or as directed by a doctor. The active ingredient, coal tar, in Psoriasin may affect very light hair color; test first on a few strands of hair before broader application to areas where light-colored hair is present. For use by normally healthy adults only; persons under 18 years of age or those with highly sensitive or allergic skin should use only as idrected by a doctor.

Other Information

You may report serious side effects to the phone number provided under Questions? below.

Inactive ingredients

Aloe vera gel, capylic/capric triglycerides, cetearyl alcohol, citric acid anhydrous, Dead Sea salts, ethanol, glycerin, glyceryl stearate SE, lavender oil, myristyl alcohol, oatmeal extract, olive oil, PEG-100 stearate, petrolatum, phenoxyethanol, polysorbate 80, shea oil, stearyl alcohol, sweet almond oil, water.

Questions?

1-800-792-2582